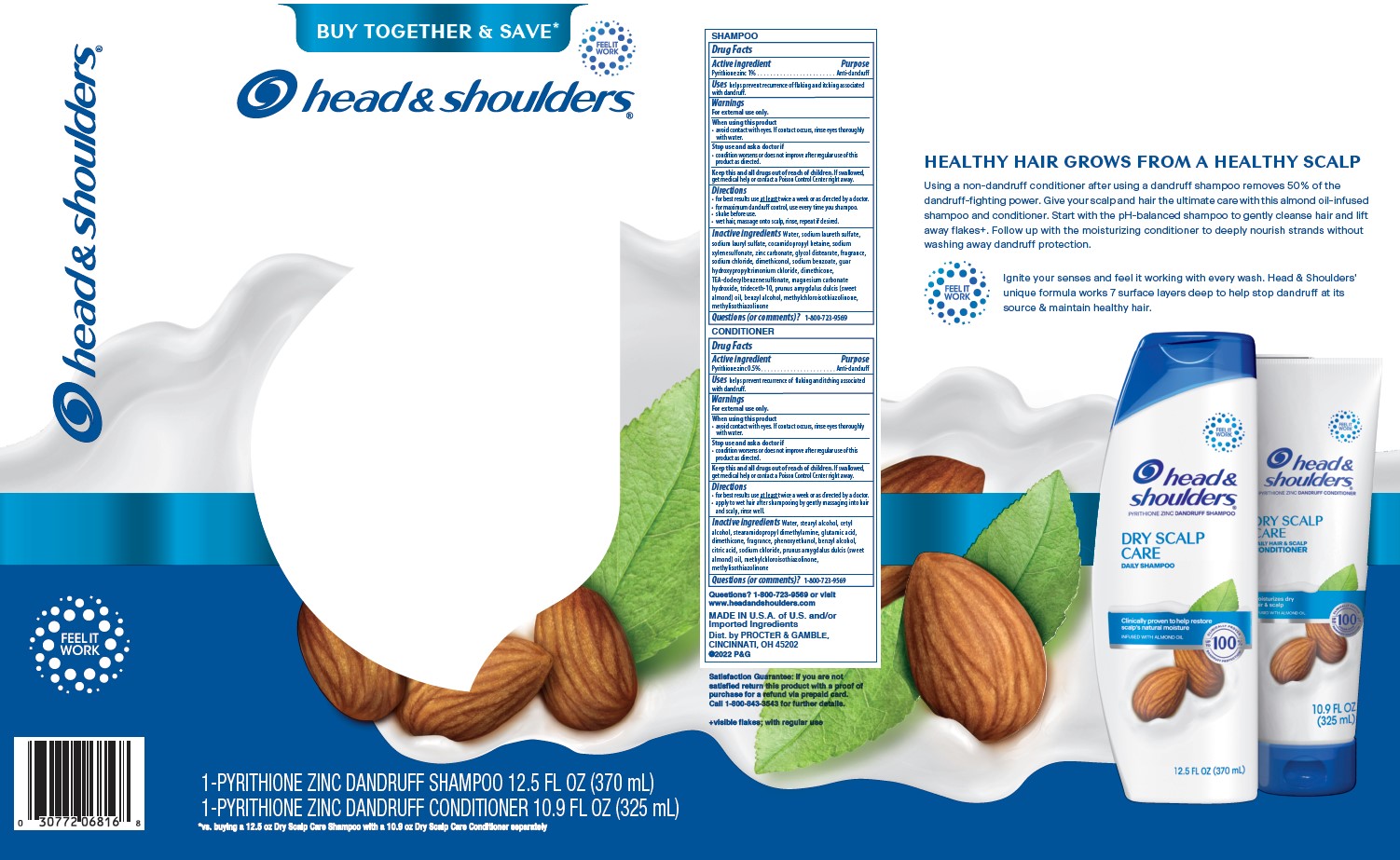 DRUG LABEL: Head and Shoulders Dry Scalp Care Dual Pack
NDC: 84126-077 | Form: KIT | Route: TOPICAL
Manufacturer: The Procter & Gamble Manufacturing Company
Category: otc | Type: HUMAN OTC DRUG LABEL
Date: 20250129

ACTIVE INGREDIENTS: PYRITHIONE ZINC 1 g/100 mL; PYRITHIONE ZINC 0.5 g/100 mL
INACTIVE INGREDIENTS: WATER; COCAMIDOPROPYL BETAINE; SODIUM CHLORIDE; DIMETHICONOL (50000 CST); SODIUM BENZOATE; PRUNUS AMYGDALUS DULCIS (SWEET ALMOND) OIL; DIMETHICONE; SODIUM LAURETH SULFATE; SODIUM LAURYL SULFATE; SODIUM XYLENESULFONATE; ZINC CARBONATE; GUAR HYDROXYPROPYLTRIMONIUM CHLORIDE; TEA-DODECYLBENZENESULFONATE; MAGNESIUM CARBONATE HYDROXIDE; BENZYL ALCOHOL; GLYCOL DISTEARATE; TRIDECETH-10; METHYLCHLOROISOTHIAZOLINONE; METHYLISOTHIAZOLINONE; STEARYL ALCOHOL; WATER; CETYL ALCOHOL; PHENOXYETHANOL; BENZYL ALCOHOL; METHYLISOTHIAZOLINONE; DIMETHICONE; CITRIC ACID; METHYLCHLOROISOTHIAZOLINONE; PRUNUS AMYGDALUS DULCIS (SWEET ALMOND) OIL; STEARAMIDOPROPYL DIMETHYLAMINE; SODIUM CHLORIDE; GLUTAMIC ACID

Head and Shoulders® Dry Scalp Care Kit

SHAMPOO

Drug Facts

Active ingredient

Pyrithione zinc 1%

Purpose

Anti-dandruff

Uses

helps prevent recurrence of flaking and itching associated with dandruff.

Warnings

For external use only.

When using this product

- avoid contact with eyes. If contact occurs, rinse eyes thoroughly with water.

Stop use and ask a doctor if

- condition worsens or does not improve after regular use of this product as directed.

KEEP OUT OF REACH OF CHILDREN

Keep this and all drugs out of reach of children.

If swallowed, get medical help or contact a Poison Control Center right away.

Directions

- for best results use at least twice a week or as directed by a doctor.
- for maximum dandruff control, use every time you shampoo.
- shake before use.
- wet hair, massage onto scalp, rinse, repeat if desired.

Inactive ingredients

Water, sodium laureth sulfate, sodium lauryl sulfate, cocamidopropyl betaine, sodium xylenesulfonate, zinc carbonate, glycol distearate, fragrance, sodium chloride, dimethiconol, sodium benzoate, guar hydroxypropyltrimonium chloride, dimethicone, TEA-dodecylbenzenesulfonate, magnesium carbonate hydroxide, trideceth-10, prunus amygdalus dulcis (sweet almond) oil, benzyl alcohol, methylchloroisothiazolinone, methylisothiazolinone

Questions (or comments)?

1-800-723-9569

CONDITIONER

Drug Facts

Active ingredient

Pyrithione zinc 0.5%

Purpose

Anti-dandruff

Uses

helps prevent recurrence of flaking and itching associated with dandruff.

Warnings

For external use only.

When using this product

- avoid contact with eyes. If contact occurs, rinse eyes thoroughly with water.

Stop use and ask a doctor if

- condition worsens or does not improve after regular use of this product as directed.

KEEP OUT OF REACH OF CHILDREN

Keep this and all drugs out of reach of children.

If swallowed, get medical help or contact a Poison Control Center right away.

Directions

- for best results use at least twice a week or as directed by a doctor.
- apply to wet hair after shampooing by gently massaging into hair and scalp, rinse well.

Inactive ingredients

Water, stearyl alcohol, cetyl alcohol, stearamidopropyl dimethylamine, glutamic acid, dimethicone, fragrance, phenoxyethanol, benzyl alcohol, citric acid, sodium chloride, prunus amygdalus dulcis (sweet almond) oil, methylchloroisothiazolinone, methylisothiazolinone

Questions (or comments)?

1-800-723-9569

Dist. by PROCTER & GAMBLE,
CINCINNATI, OH 45202

PRINCIPAL DISPLAY PANEL - Kit

head & shoulders ®

Shampoo & Conditioner Inside

head & shoulders

pyrithione zinc dandruff shampoo

DRY SCALP CARE

DAILY SHAMPOO

head & shoulders

pyrithione zinc dandruff conditioner

DRY SCALP CARE DAILY HAIR & SCALP

CONDITIONER

1 PYRITHIONE ZINC DANDRUFF

SHAMPOO 12.5 FL OZ (370 mL)

1 PYRITHIONE ZINC DANDRUFF

CONDITIONER 10.9 FL OZ (325 mL)